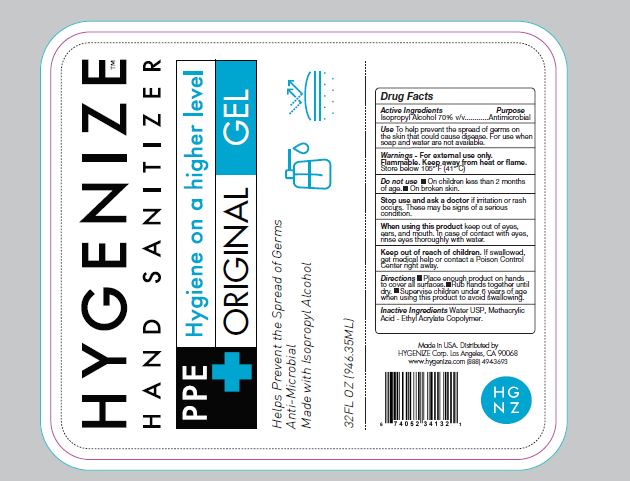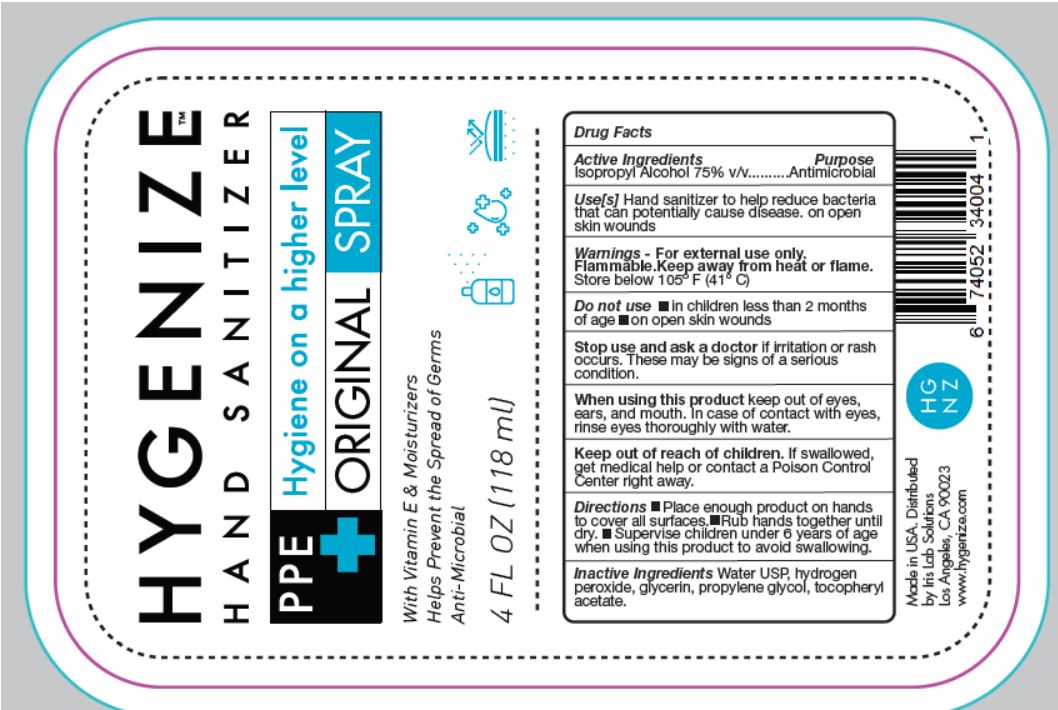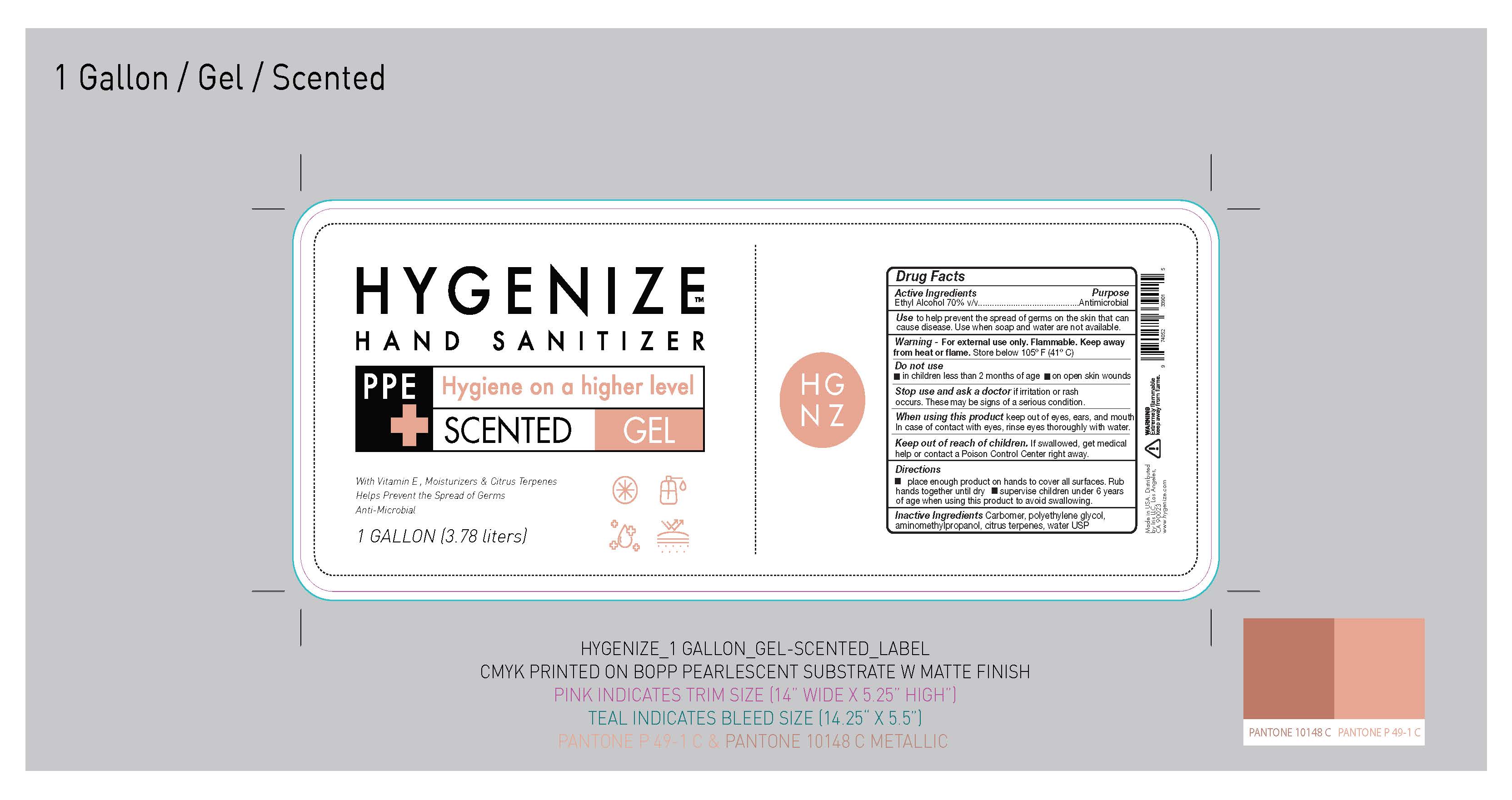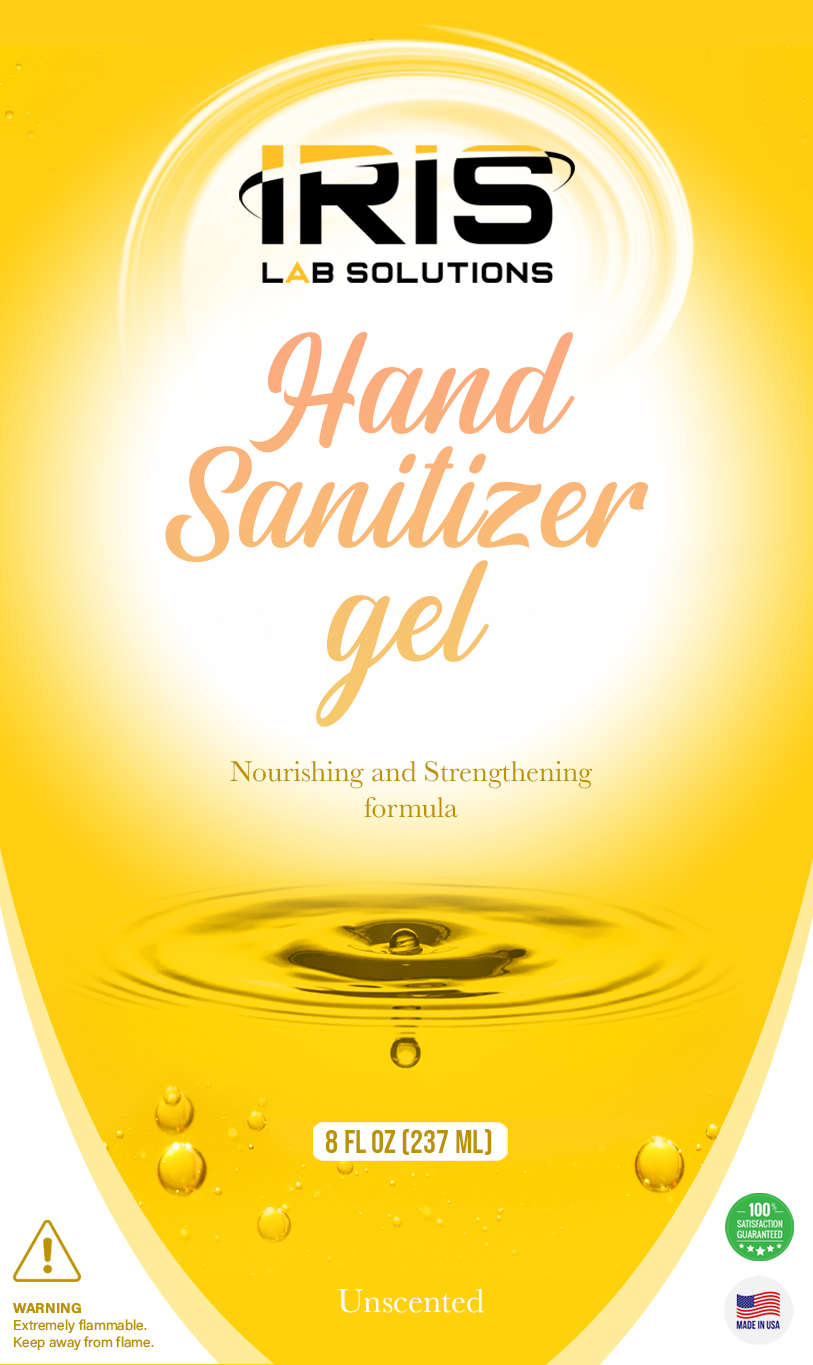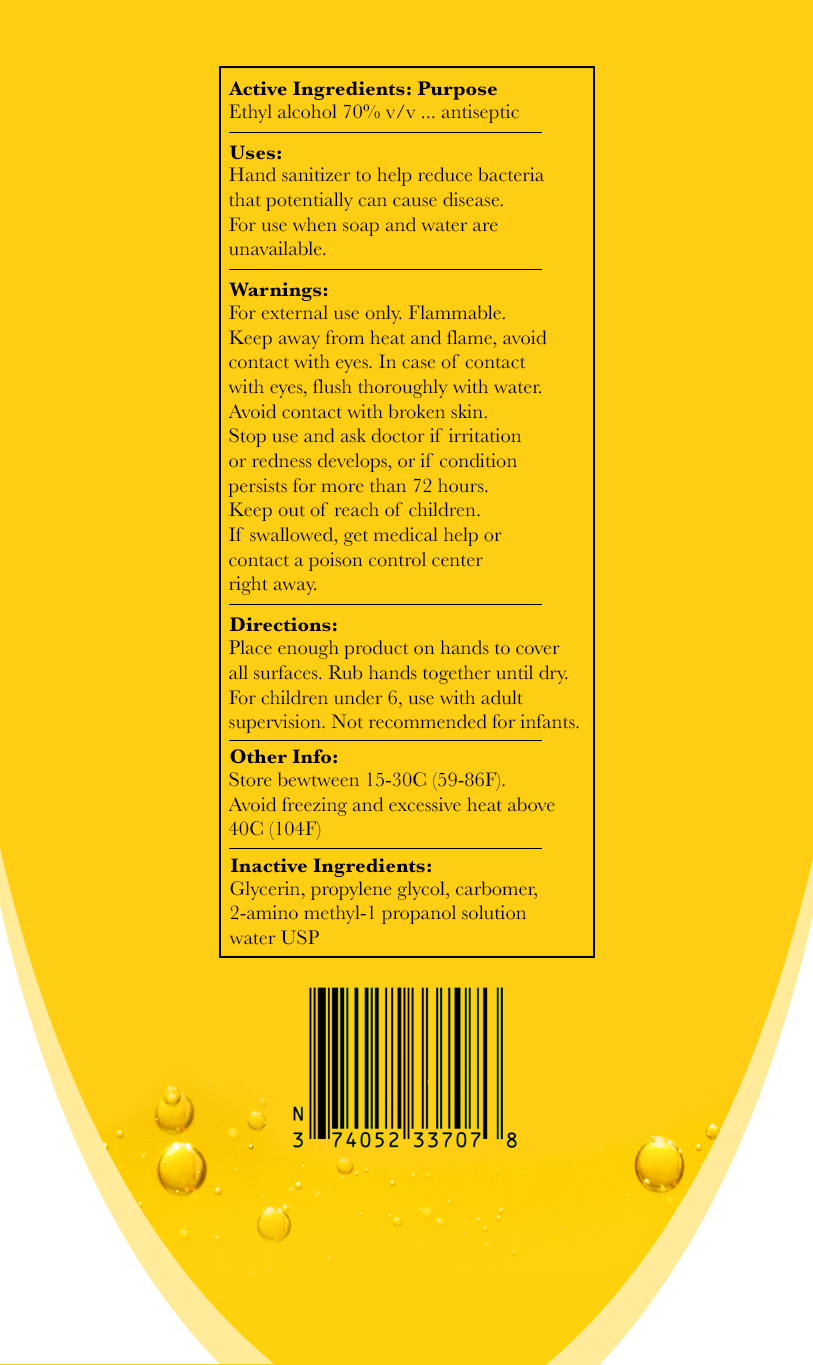 DRUG LABEL: Hygenize Hand Sanitizer
NDC: 74052-339 | Form: GEL
Manufacturer: Iris LLC
Category: otc | Type: HUMAN OTC DRUG LABEL
Date: 20201003

ACTIVE INGREDIENTS: ALCOHOL 70 mL/100 mL
INACTIVE INGREDIENTS: WATER; METHACRYLIC ACID - ETHYL ACRYLATE COPOLYMER (1:1) TYPE A

ACTIVE INGREDIENT

Alcohol 70% v/v. Purpose: Antiseptic

PURPOSE

Antiseptic, Hand Sanitizer

INDICATIONS AND USAGE

Hand Sanitizer to help reduce bacteria that potentially can cause disease. For use when soap and water are not available.

WARNINGS

For external use only. Flammable. Keep away from heat and flame.

DO NOT USE

In children less than two months of age

On open skin wounds

When using this product keep out of eyes, ears, and mouth. In case of contact with eyes, rinse eyes thoroughly with water.

Stop use and ask a doctor if irritation or rash occurs. These may be signs of a serious condition.

Keep out of reach of children. If swallowed, get medical help or contact a Poison Control Center right away.

Stop use and ask a doctor if irritation or rash occurs. These may be signs of a serious condition.

Keep out of reach of children. If swallowed, get medical help or contact a Poison Control Center right away.

DOSAGE AND ADMINISTRATION

Place enough product on hands to cover all surfaces. Rub hands together until dry.

Supervise children under 6 years of age when using this product to avoid swallowing.

STORAGE AND HANDLING

Store between 15-30C (59-86F)

Avoid freezing and excessive heat above 40C (104F)

INACTIVE INGREDIENT

Glycerin, propylene glycol, carbomer, aminomethylproponal, purified water USP

PACKAGE LABEL

8 FL OZ (237 ML)

118 ml NDC: 74052-340-04

946.353 ml NDC: 74052-341-32